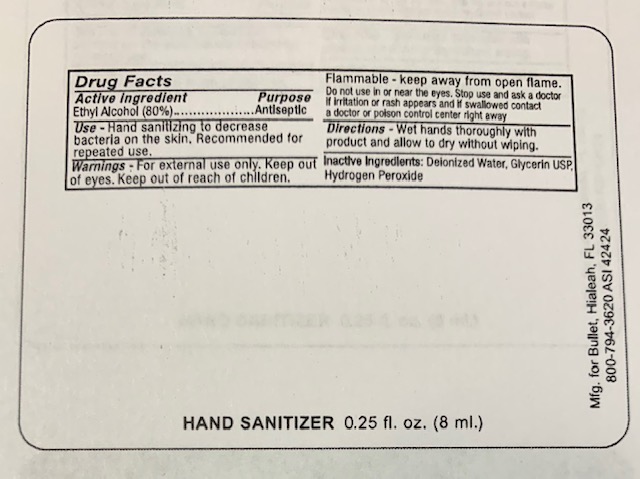 DRUG LABEL: Hand Sanitizer								
NDC: 19392-150 | Form: LIQUID
Manufacturer: Bullet Line, LLC
Category: otc | Type: HUMAN OTC DRUG LABEL
Date: 20200821

ACTIVE INGREDIENTS: ALCOHOL 800 mL/1000 mL
INACTIVE INGREDIENTS: WATER; GLYCERIN; HYDROGEN PEROXIDE

Drug Facts

ACTIVE INGREDIENT

Ethyl Alcohol (80%)

PURPOSE

Antiseptic

INDICATIONS AND USAGE

Hand sanitizing to reduce bacteria on the skin. Recommended for repeated use.

WARNINGS

For external use only. Keep out of eyes. Keep out of reach of children. Flammable - keep away from open flame. Do not use in or near the eyes. Stop use and ask a doctor if irritation or rash appears and if swallowed contact a doctor or poison control center right away.

INACTIVE INGREDIENT

Glycerin, Hydrogen Peroxide, Purified Water USP

DOSAGE AND ADMINISTRATION

Wet hands thoroughly with product and allow to dry without wiping.

Keep out of reach of children